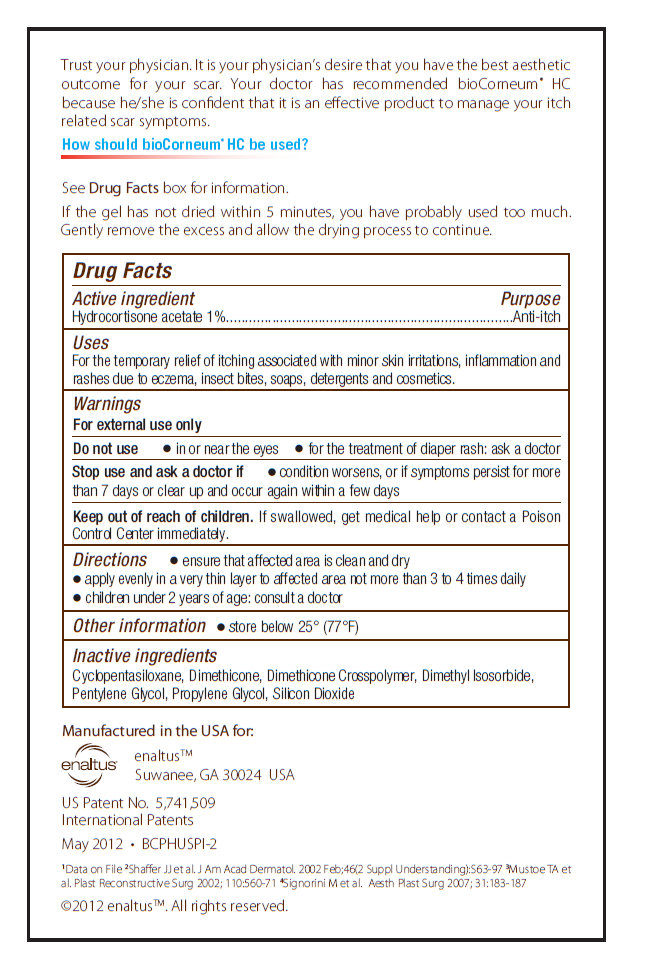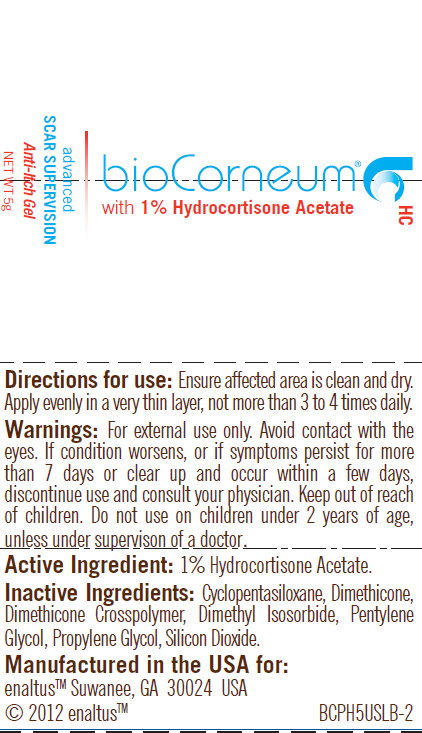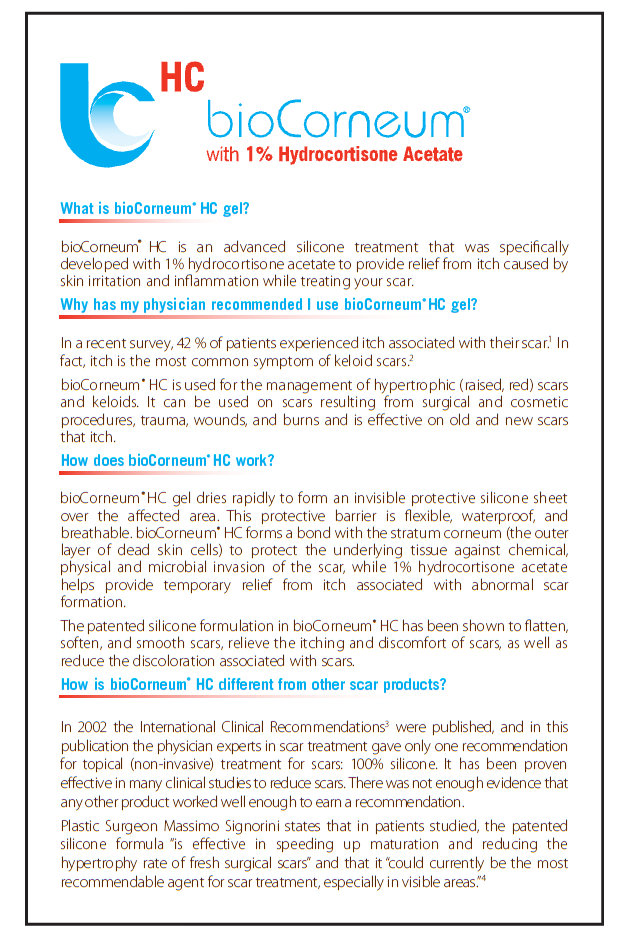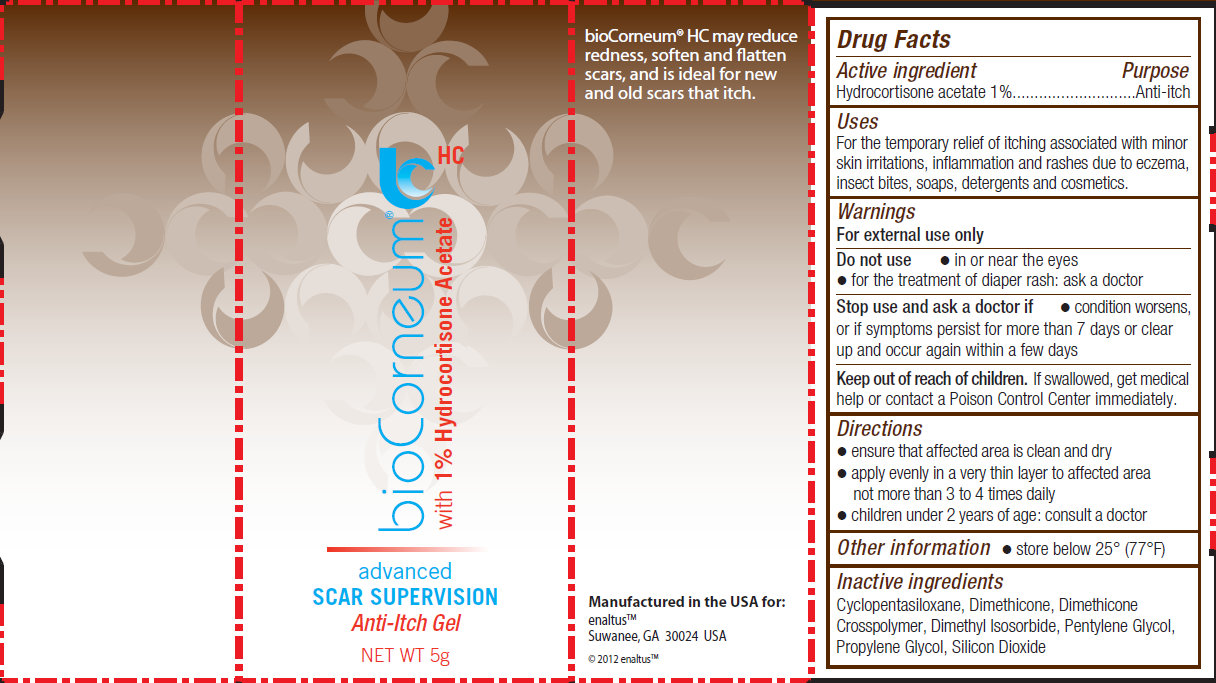 DRUG LABEL: bioCorneum HC Advanced Scar Supervision Anti-Itch
NDC: 43474-000 | Form: GEL
Manufacturer: Enaltus Inc
Category: otc | Type: HUMAN OTC DRUG LABEL
Date: 20120516

ACTIVE INGREDIENTS: HYDROCORTISONE ACETATE 1 g/100 g
INACTIVE INGREDIENTS: CYCLOMETHICONE 5; DIMETHICONE; DIMETHYL ISOSORBIDE; PENTYLENE GLYCOL; PROPYLENE GLYCOL; SILICON DIOXIDE

bioCorneum HC Advanced Scar Supervision Anti-Itch Gel

Active ingredient

Hydrocortisone acetate 1%

Purpose

Anti-itch

Uses

For the temporary relief of itching associated with minor skin irritations, inflammation and rashes due to eczema, insect bites, soaps, detergents and cosmetics.

Warnings

For external use only

Do not use

- in or near the eyes
- for the treatment of diaper rash: ask a doctor

Stop use and ask a doctor if

- condition worsens, or if symptoms persist for more than 7 days or clear up and occur again within a few days

Keep out of reach of children

If swallowed, get medical help or contact a Poison Control Center immediately.

Directions

- ensure that affected area is clean and dry
- apply evenly in a very thin layer to affected area not more than 3 to 4 times daily
- children under 2 years of age : consult a doctor

Other information

- store below 25 degree (77 degree F)

Inactive ingredients

Cyclopentasiloxane, Dimethicone, Dimethicone Crosspolymer, Dimethyl Isosorbide, Pentylene Glycol, Propylene Glycol, Silicon Dioxide